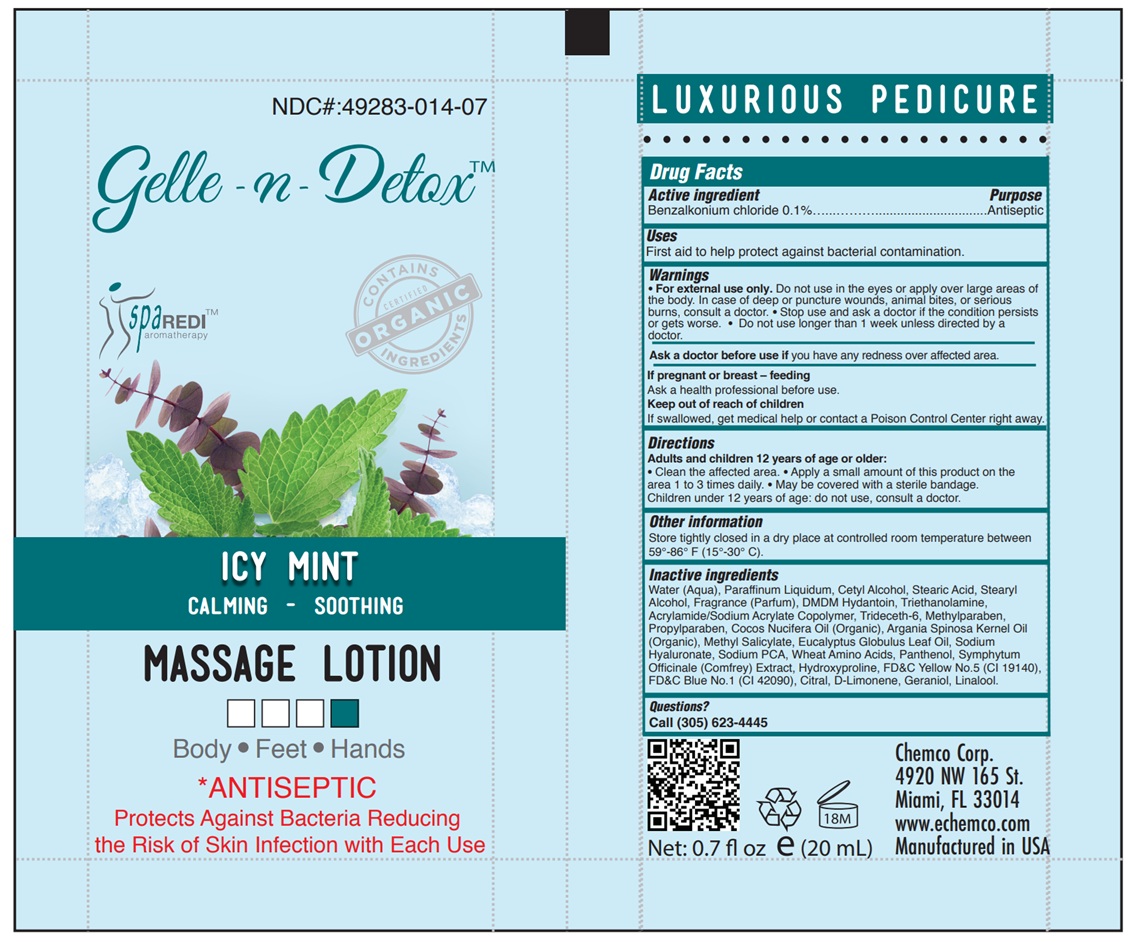 DRUG LABEL: GELLE-N-DETOX ICE MINT AND EUCALYPTUS MASSAGE
NDC: 49283-014 | Form: LOTION
Manufacturer: CHEMCO CORPORATION
Category: otc | Type: HUMAN OTC DRUG LABEL
Date: 20251204

ACTIVE INGREDIENTS: BENZALKONIUM CHLORIDE 0.1 g/100 g
INACTIVE INGREDIENTS: CARBOMER HOMOPOLYMER TYPE C; TRIDECETH-6; HYALURONATE SODIUM; SODIUM PYRROLIDONE CARBOXYLATE; AMINO ACIDS, WHEAT; SYMPHYTUM OFFICINALE WHOLE; FD&C BLUE NO. 1; CITRAL; LIMONENE, (+)-; WATER; STEARYL ALCOHOL; METHYL SALICYLATE; PANTHENOL; EUCALYPTUS OIL; MINERAL OIL; STEARIC ACID; TROLAMINE; PROPYLPARABEN; ARGAN OIL; FD&C YELLOW NO. 5; COCONUT OIL; METHYLPARABEN; DMDM HYDANTOIN; HYDROXYPROLINE; GERANIOL; LINALOOL, (+)-

49283-014-07

ACTIVE INGREDIENT

Benzalkonium Chloride 0.1%

PURPOSE

Antiseptic

Uses

First aid to help protect against bacterial contamination.

WARNINGS

- For external use only.
- Do not use in the eyes or apply over large areas of the body.
- In case of deep or puncture wounds, animal bites, or serious burns, consult a doctor.
- Stop use and ask a doctor if the condition persists or gets worse.
- Do not use longer than 1 week unless directed by a doctor

Ask a doctor before use if you have redness over affected area.

PREGNANCY OR BREAST FEEDING

Ask a health professional before use.

KEEP OUT OF REACH OF CHILDREN

If swallowed, get medical help or contact a Poison Control Center
right away

Directions

Adults and children 12 years of age or older: • Clean the affected area. • Apply a small amount of this product on the area 1 to 3 times daily. • May be covered with a sterile bandage. Children under 12 years of age: do not use, consult a doctor.

OTHER SAFETY INFORMATION

Store tightly closed in a dry place at controlled room temperature between 59°-86° F (15°-30° C).

INACTIVE INGREDIENT

Water (Aqua), Paraffinum Liquidum, Cetyl Alcohol, Stearic Acid, Stearyl Alcohol, Fragrance (Parfum), DMDM Hydantoin, Triethanolamine, Acrylamide/Sodium Acrylate Copolymer, Trideceth-6, Methylparaben, Propylparaben, Cocos Nucifera Oil (Organic), Argania Spinosa Kernel Oil (Organic), Methyl Salicylate, Eucalyptus Globulus Leaf Oil, Sodium Hyaluronate, Sodium PCA, Wheat Amino Acids, Panthenol, Symphytum Officinale (Comfrey) Extract, Hydroxyproline, FD&C Yellow No.5 (CI 19140), FD&C Blue No.1 (CI 42090), Citral, D-Limonene, Geraniol, Linalool.

QUESTIONS

Call (305) 623-4445